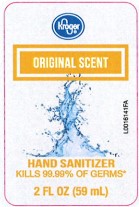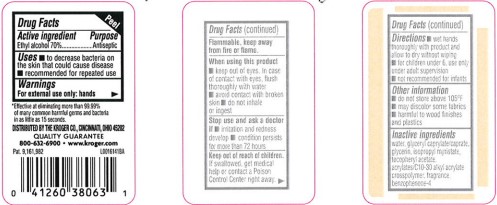 DRUG LABEL: Hand Sanitizer
NDC: 30142-596 | Form: GEL
Manufacturer: The Kroger Co.
Category: otc | Type: HUMAN OTC DRUG LABEL
Date: 20260227

ACTIVE INGREDIENTS: ALCOHOL 70 mL/100 mL
INACTIVE INGREDIENTS: WATER; GLYCERYL CAPRYLATE/CAPRATE; GLYCERIN; ISOPROPYL MYRISTATE; .ALPHA.-TOCOPHEROL ACETATE; CARBOMER INTERPOLYMER TYPE A (ALLYL SUCROSE CROSSLINKED); SULISOBENZONE

Kroger 370.001/370AE rev 1
Advanced Hand Sanitizer

Active ingredient

Ethyl Alcohol 70%

Purpose

Antiseptic

Uses

- to decrease bacteria on the skin that could cause disease
- recommended for repeated use

Warnings

For external use only: hands

Flammable, keep away from fire or flame.

When using this product

- keep out of eyes. In case of contact with eyes, flush thoroughly with water.
- avoid contact with broken skin
- do not inhale or ingest

Stop use and ask a doctor

- irritation and redness develop
- condition persists for more than 72 hours

Keep out of reach of children.

If swallowed, get medical help or contact a Poison Control Center right away.

Directions

- wet hands thoroughly with product and allow to dry without wiping
- for children under 6, use only under adult supervision
- not recommended for infants

Other information

- do not store above 105⁰F
- may discolor some fabrics
- harmful to wood finishes and plastics

Inactive ingredients

water ,glyceryl caprylate/caprate ,glycerin ,isopropyl myristate ,tocopheryl acetate ,acrylates/C10-30 alkyl acrylate crosspolymer, fragrance ,benzophenone-4

Claim

*Effective at eliminating more than 99.99% of many common harmful germs and bacteria in as little as 15 seconds.

ADVERSE REACTION

DISTRIBUTED BY: KROGER CO

CINCINNATI, OHIO 45202

QUALITY GUARANTEE

800-632-6900 www.kroger.com

Pat. 9,161,982

Principal display panel

Kroger®

ORIGINAL SCENT

HAND SANITIZER

KILLS 99.99% OF GERMS*

2 FL OZ (59 mL)